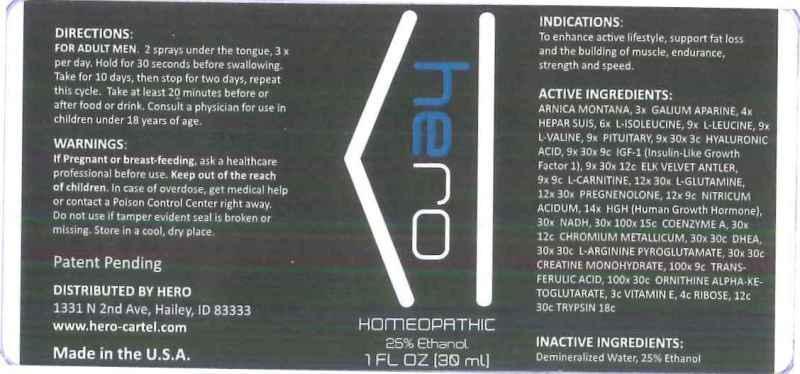 DRUG LABEL: Hero
NDC: 49291-0002 | Form: LIQUID
Manufacturer: Hero
Category: homeopathic | Type: HUMAN OTC DRUG LABEL
Date: 20131015

ACTIVE INGREDIENTS: ARNICA MONTANA 3 [hp_X]/1 mL; GALIUM APARINE 4 [hp_X]/1 mL; PORK LIVER 6 [hp_X]/1 mL; ISOLEUCINE 9 [hp_X]/1 mL; LEUCINE 9 [hp_X]/1 mL; VALINE 9 [hp_X]/1 mL; SUS SCROFA PITUITARY GLAND 9 [hp_X]/1 mL; HYALURONIC ACID 9 [hp_X]/1 mL; MECASERMIN 9 [hp_X]/1 mL; CERVUS ELAPHUS VELVET 9 [hp_X]/1 mL; LEVOCARNITINE 12 [hp_X]/1 mL; GLUTAMINE 12 [hp_X]/1 mL; PREGNENOLONE 12 [hp_X]/1 mL; NITRIC ACID 14 [hp_X]/1 mL; SOMATROPIN 30 [hp_X]/1 mL; NADH 30 [hp_X]/1 mL; COENZYME A 30 [hp_X]/1 mL; CHROMIUM 30 [hp_X]/1 mL; PRASTERONE 30 [hp_X]/1 mL; ARGININE PYROGLUTAMATE 30 [hp_X]/1 mL; CREATINE MONOHYDRATE 100 [hp_X]/1 mL; FERULIC ACID 100 [hp_X]/1 mL; ORNITHINE .ALPHA.-KETOGLUTARATE 3 [hp_C]/1 mL; .ALPHA.-TOCOPHEROL 4 [hp_C]/1 mL; RIBOSE, D- 12 [hp_C]/1 mL; TRYPSIN 18 [hp_C]/1 mL
INACTIVE INGREDIENTS: WATER; ALCOHOL

DRUG FACTS:

ACTIVE INGREDIENTS:

Arnica Montana 3X, Galium Aparine 4X, Hepar Suis 6X, L-Isolucine 9X, L-Leucine 9X, L-Valine 9X, Pituitary (Suis) 9X, 30X, 3C, Hyaluronic Acid 9X, 30X, 9C, IGF-1 9X, 30X, 12C, Elk Velvet Antler 9X, 9C, L-Carnitine 12X, 30X, L-Glutamine 12X, 30X, Pregnenolone 12X, 9C, Nitricum Acidum 14X, HGH 30X, NADH-S 30X, 100X, 15C, Coenzyme A 30X, 12C, Chromium Metallicum 30X, 30C, DHEA 30X, 30C, L-Arginine Pyroglutamate 30X, 30C, Creatine Monohydrate 100X, 9C, Trans-Ferulic Acid 100X, 30C, Ornithine Alpha-Ketoglutarate 3C, Vitamin E 4C, Ribose 12C, 30C, Trypsin 18C.

INDICATIONS:

To enhance active lifestyle, support fat loss and the building of muscle, endurance, strength and speed.

WARNINGS:

If pregnant or breast-feeding, ask a healthcare professional before use. Keep out of the reach of children. In case of overdose, get medical help or contact a Poison Control Center right away. Do not use if tamper evident seal is broken or missing. Store in a cool, dry place.

KEEP OUT OF REACH OF CHILDREN:

Keep out of the reach of children. In case of overdose, get medical help or contact a Poison Control Center right away.

DIRECTIONS:

FOR ADULT MEN: 2 sprays under the tongue, 3 x per day. hold for 30 seconds before swallowing. Take for 10 days, then stop for two days, repeat this cycle. Take at least 20 minutes before or after food or drink. Consult a physician for use in children under 18 years of age.

INDICATIONS:

To enhance active lifestyle, support fat loss and the building of muscle, endurance, strength and speed.

INACTIVE INGREDIENTS:

Demineralized Water, Ethanol 25%

QUESTIONS:

DISTRIBUTED BY HERO

1331 N 2nd Ave, Hailey, ID 83333

www.hero-cartel.com

Made in the U.S.A.

PACKAGE DISPLAY LABEL:

hero

HOMEOPATHIC

25% Ethanol

1 FL OZ (30 mL)